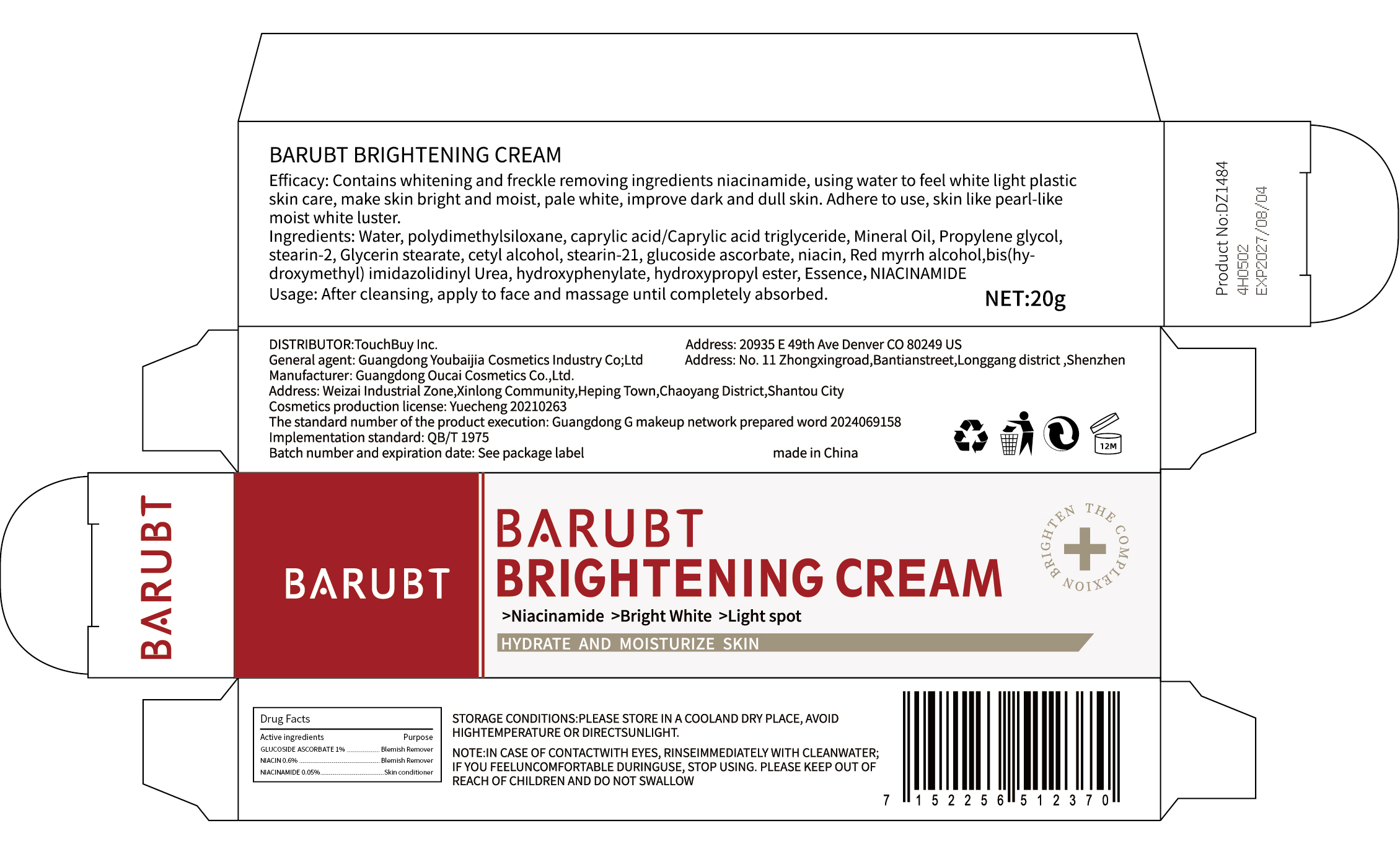 DRUG LABEL: BARUBT BRIGHTENING
NDC: 84712-001 | Form: CREAM
Manufacturer: Guangdong Youbaijia Cosmetic Industry Co., Ltd
Category: otc | Type: HUMAN OTC DRUG LABEL
Date: 20240904

ACTIVE INGREDIENTS: NIACINAMIDE 0.01 g/20 g; NIACIN 0.12 g/20 g
INACTIVE INGREDIENTS: WATER 14.768 g/20 g; MINERAL OIL 0.7 g/20 g

Active Ingredients

glucoside ascorbate 1%

niacin 0.6%

NIACINAMIDE 0.05%

Purpose

whitening and freckle removing, brightening skin

Uses

After cleansing, apply to face and massage until completely absorbed.

Warnings

For external use only. Keep out of the reach of children.Avoid contact with eyes.

Stop use

Discontinue use if signs of irritation or rash occur.

Do not use

on damaged or broken skin

Keep out of reach of children

If swallowed, get medical help or contact a Poison Control Center right away

When using this product

keep out of eyes. Rinse with water to remove

DOSAGE & ADMINISTRATION

- well cleansing your face
- apply mean brightening cream to face and massage until completely absorbed.
- children under 6 months ofage: Ask a doctor

Inactive ingredient

Water
polydimethylsiloxane
caprylic acid/Caprylic acid triglyceride
Mineral Oil
Propylene glycol
stearin-2
Glycerin stearate
cetyl alcohol
stearin-21
Red myrrh alcohol
bis(hydroxymethyl) imidazolidinyl Urea
hydroxyphenylate
hydroxypropyl ester
Essence

Storage and handling

Store in a cool and dry place.

Questions

Company phone number: +1 818 579 7288
Company e-mail: jessie@registeragentllc.com